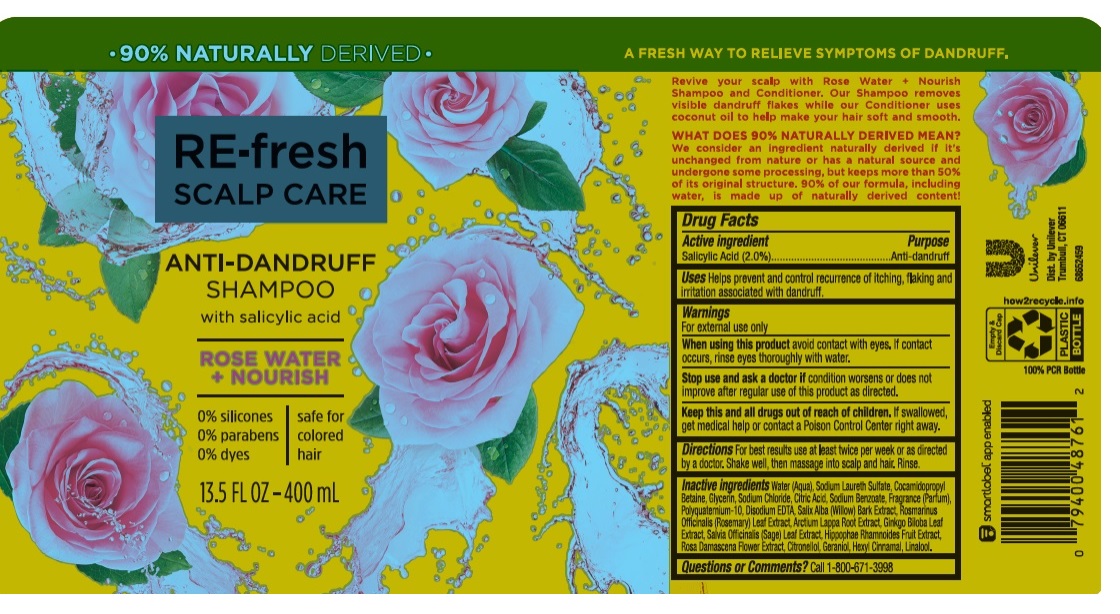 DRUG LABEL: RE-fresh Scalp Care
NDC: 64942-1928 | Form: SHAMPOO
Manufacturer: Conopco, Inc. d/b/a/ Unilever
Category: otc | Type: HUMAN OTC DRUG LABEL
Date: 20241107

ACTIVE INGREDIENTS: SALICYLIC ACID 2 g/100 mL
INACTIVE INGREDIENTS: HIPPOPHAE RHAMNOIDES FRUIT; .BETA.-CITRONELLOL, (R)-; WATER; SODIUM LAURETH SULFATE; COCAMIDOPROPYL BETAINE; SODIUM CHLORIDE; GLYCERIN; SAGE; ARCTIUM LAPPA ROOT; GINKGO; SODIUM BENZOATE; POLYQUATERNIUM-10 (1000 MPA.S AT 2%); EDETATE DISODIUM ANHYDROUS; ROSEMARY; ROSA X DAMASCENA FLOWER; SALIX ALBA BARK; CITRIC ACID MONOHYDRATE; GERANIOL; .ALPHA.-HEXYLCINNAMALDEHYDE; LINALOOL, (+/-)-

RE-fresh Scalp Care Rose Water + Nourish Anti-Dandruff Shampoo

Drug Facts

Active ingredient

Salicylic Acid (2.0%)

Purpose

Anti-dandruff

Use

Helps prevent and control recurrence of itching, flaking and irritation associated with dandruff.

Warnings

For external use only
When using this product Avoid contact with eyes. If contact occurs, rinse eyes thoroughly with water.
Stop use and ask a doctor if: Condition worsens or does not improve after regular use of this product as directed.

KEEP OUT OF REACH OF CHILDREN

• Keep this and all drugs out of reach of children.
If swallowed, get medical help or contact a Poison Control Center right away.

Directions

For best results use at least twice per week or as directed by a doctor. Massage into scalp and hair. Rinse.

Inactive Ingredients

Water (Aqua), Sodium Laureth Sulfate, Cocamidopropyl Betaine, Glycerin, Sodium Chloride, Citric Acid, Sodium Benzoate, Fragrance (Parfum), Polyquaternium-10, Disodium EDTA, Salix Alba (Willow) Bark Extract, Rosmarinus Officinalis (Rosemary) Leaf Extract, Arctium Lappa Root Extract, Ginkgo Biloba Leaf Extract, Salvia Officinalis (Sage) Leaf Extract, Hippophae Rhamnoides Fruit Extract, Rosa Damascena Flower Extract, Citronellol, Geraniol, Hexyl Cinnamal, Linalool.

Questions/comments?

Call toll-free 1-800-671-3998